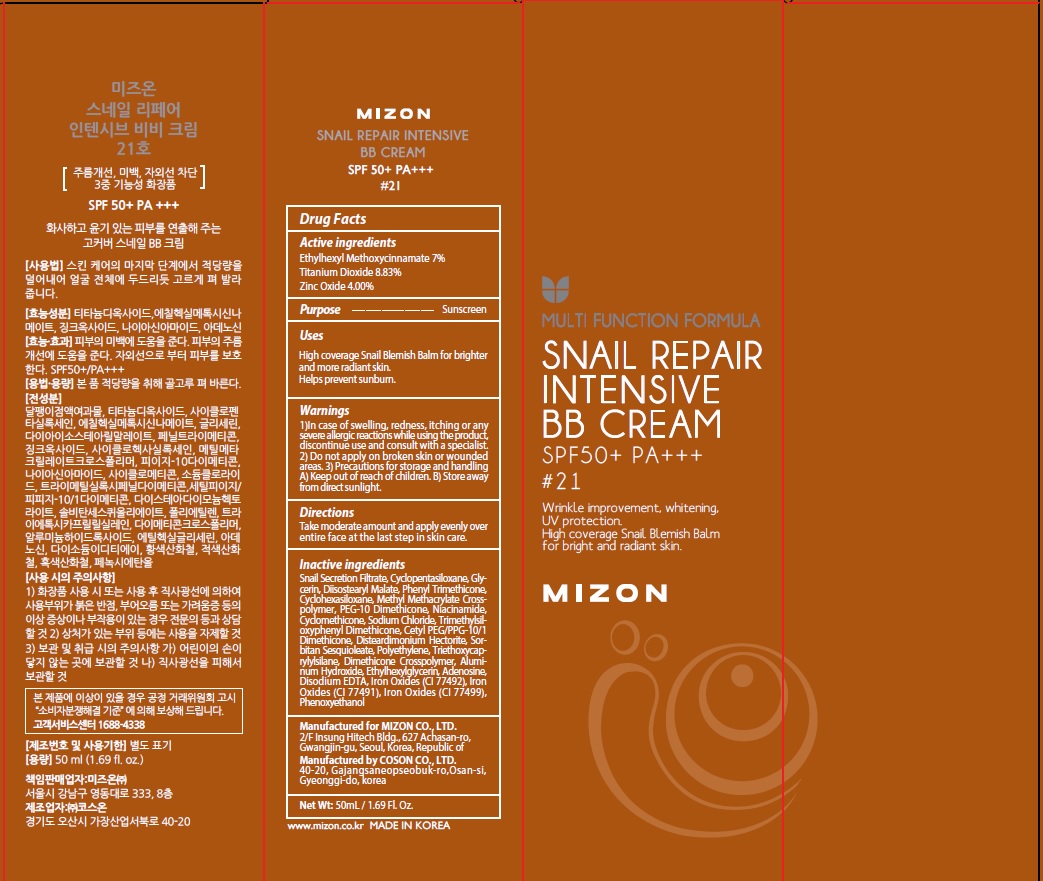 DRUG LABEL: MIZON SNAIL REPAIR INTENSIVE BB 21
NDC: 57718-390 | Form: CREAM
Manufacturer: MIZON CO.,LTD.
Category: otc | Type: HUMAN OTC DRUG LABEL
Date: 20200120

ACTIVE INGREDIENTS: Octinoxate 3.50 g/50 mL; Titanium Dioxide 4.41 g/50 mL; Zinc Oxide 2.00 g/50 mL
INACTIVE INGREDIENTS: Glycerin; Diisostearyl Malate

ACTIVE INGREDIENT

Active ingredients: Ethylhexyl Methoxycinnamate 7%, Titanium Dioxide 8.83%, Zinc Oxide 4.00%

INACTIVE INGREDIENT

Inactive ingredients:
Snail Secretion Filtrate, Cyclopentasiloxane, Glycerin, Diisostearyl Malate, Phenyl Trimethicone, Cyclohexasiloxane, Methyl Methacrylate Crosspolymer, PEG-10 Dimethicone, Niacinamide, Cyclomethicone, Sodium Chloride, Trimethylsiloxyphenyl Dimethicone, Cetyl PEG/PPG-10/1 Dimethicone, Disteardimonium Hectorite, Sorbitan Sesquioleate, Polyethylene, Triethoxycaprylylsilane, Dimethicone Crosspolymer, Aluminum Hydroxide, Ethylhexylglycerin, Adenosine, Disodium EDTA, Iron Oxides (CI 77492), Iron Oxides (CI 77491), Iron Oxides (CI 77499), Phenoxyethanol

PURPOSE

Purpose: Sunscreen

WARNINGS

1)In case of swelling, redness, itching or any severe allergic reactions while using the product, discontinue use and consult with a specialist.
2) Do not apply on broken skin or wounded areas.
3) Precautions for storage and handling
A) Keep out of reach of children.
B) Store away from direct sunlight.

DESCRIPTION

Uses:

High coverage Snail Blemish Balm for brighter and more radiant skin. Helps prevent sunburn.

Directions:

Take moderate amount and apply evenly over entire face at the last step in skin care.